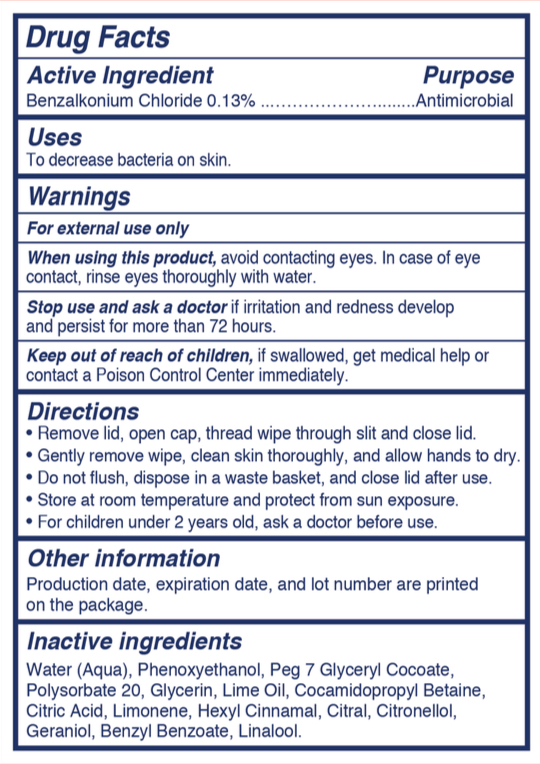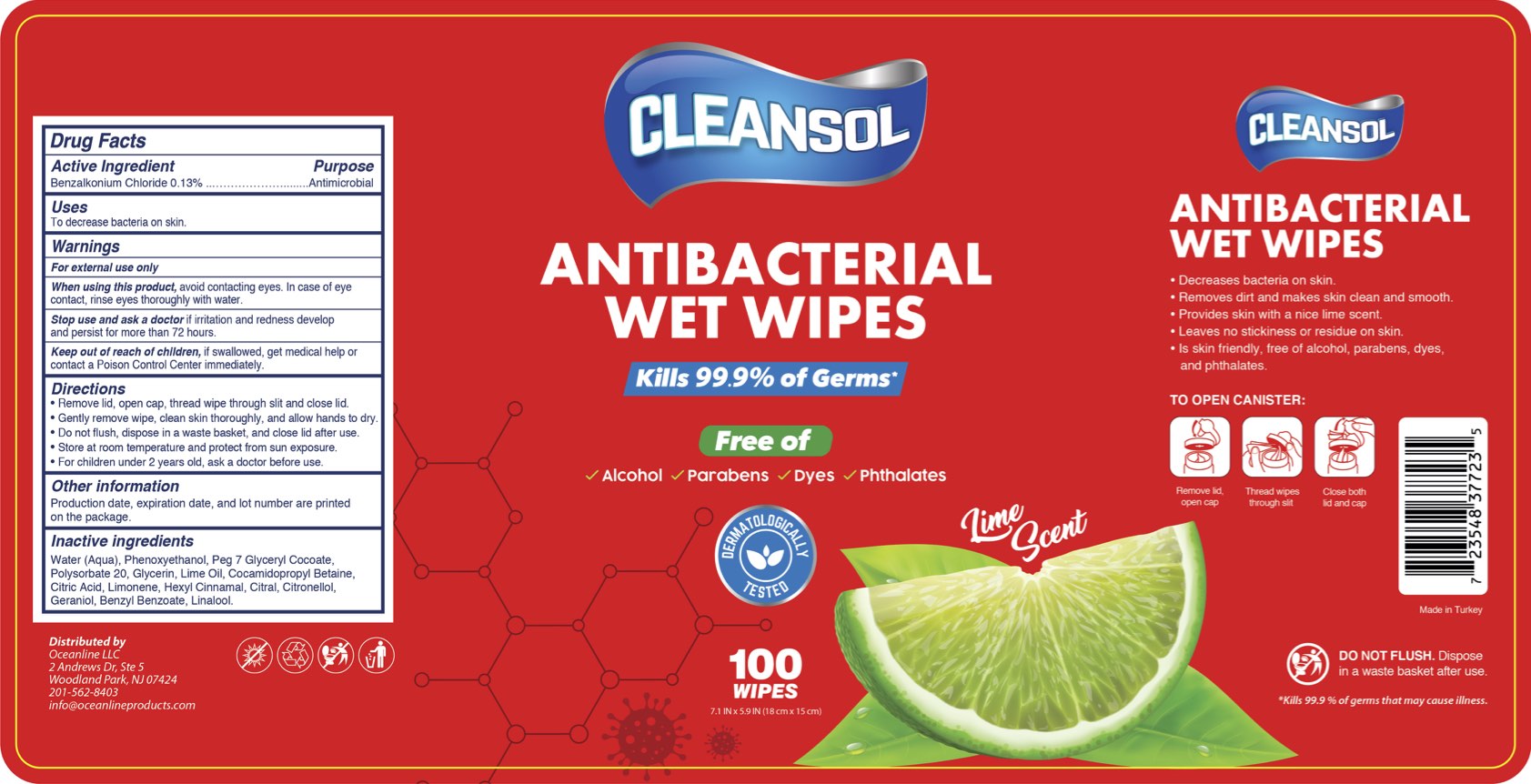 DRUG LABEL: Cleansol Antibacterial Wet Wipes
NDC: 84247-002 | Form: CLOTH
Manufacturer: Oceanline LLC
Category: otc | Type: HUMAN OTC DRUG LABEL
Date: 20240409

ACTIVE INGREDIENTS: BENZALKONIUM CHLORIDE 0.13 g/100 g
INACTIVE INGREDIENTS: POLYSORBATE 20; CITRIC ACID MONOHYDRATE; LIMONENE, (+)-; LINALOOL, (+/-)-; PEG-7 GLYCERYL COCOATE; WATER; .ALPHA.-HEXYLCINNAMALDEHYDE; LIME OIL; GERANIOL; BENZYL BENZOATE; CITRAL; .BETA.-CITRONELLOL, (R)-; COCAMIDOPROPYL BETAINE; PHENOXYETHANOL; GLYCERIN

Active Ingredient

Benzalkonium Chloride 0.13%

Purpose

Antibacterial

Uses

To decrease bacteria on skin

Warnings

For external use only

When using this product, avoid contacting eyes. In cases of eye contact, rinse eyes thoroughly with water

Stop use and ask a doctor if irritation and redness develop and persist for more than 72 hours

Keep out of reach of children, if swallowed, get medical help or contact a Poison Control Center immediately

Directions

- Remove lid, open cap, thread wipe through slit and close lid
- Gently remove wipe, clean skin thoroughly, and allow hands to dry
- Do not flush, dispose in a waste basket, and close lid after use
- Store at room temperature and protect from sun exposure
- For children under 2 years old, ask a doctor before use

Other Information

Production date, expiration date, and lot number are printed on the package

Inactive Ingredients

Water, Phenoxyethanol, Peg 7 Glyceryl Cocoate, Polysorbate 20, Glycerin, Perfume (Lime Oil), Cocamidopropyl Betaine, Citric Acid, Limonene, Hexyl Cinnamal, Citral, Citronellol, Geraniol, Benzyl Benzoate, Linalool